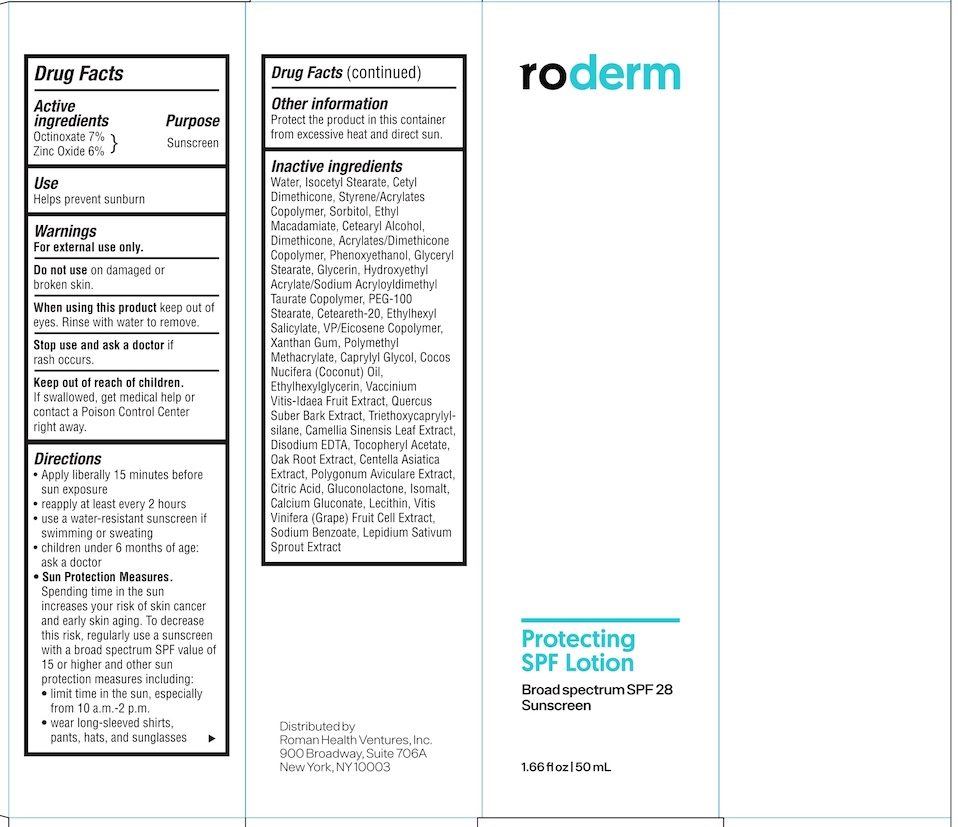 DRUG LABEL: Roderm Protecting SPF 28 Sunscreen
NDC: 72484-203 | Form: LOTION
Manufacturer: Roman Health Ventures Inc.
Category: otc | Type: HUMAN OTC DRUG LABEL
Date: 20211111

ACTIVE INGREDIENTS: OCTINOXATE 7 g/100 mL; ZINC OXIDE 6 g/100 mL
INACTIVE INGREDIENTS: POLYGONUM AVICULARE WHOLE; GLYCERYL MONOSTEARATE; POLY(METHYL METHACRYLATE; 450000 MW); COCONUT OIL; EDETATE DISODIUM; ALPHA-TOCOPHEROL ACETATE; STYRENE/ACRYLAMIDE COPOLYMER (MW 500000); DIMETHICONE; PEG-100 STEARATE; CETYL DIMETHICONE 150; ISOCETYL STEARATE; WATER; CAPRYLYL GLYCOL; ETHYLHEXYLGLYCERIN; VACCINIUM VITIS-IDAEA FRUIT OIL; LEPIDIUM SATIVUM WHOLE; SORBITOL; ETHYL MACADAMIATE; POLYOXYL 20 CETOSTEARYL ETHER; XANTHAN GUM; VINYLPYRROLIDONE/EICOSENE COPOLYMER; QUERCUS SUBER BARK; CETOSTEARYL ALCOHOL; PHENOXYETHANOL; GLYCERIN; HYDROXYETHYL ACRYLATE/SODIUM ACRYLOYLDIMETHYL TAURATE COPOLYMER (45000 MPA.S AT 1%); OCTISALATE; CITRIC ACID MONOHYDRATE; GLUCONOLACTONE; CALCIUM GLUCONATE; LECITHIN, SOYBEAN; VITIS VINIFERA FRUIT OIL; SODIUM BENZOATE; QUERCUS SPP. WHOLE; TRIETHOXYCAPRYLYLSILANE; GREEN TEA LEAF; CENTELLA ASIATICA; ISOMALT; VINYL DIMETHICONE/METHICONE SILSESQUIOXANE CROSSPOLYMER

Roderm Protecting SPF Lotion

Drug Facts

Active ingredients

Octinoxate 7%

Zinc Oxide 6%

Purpose

Sunscreen

Use

Helps prevent sunburn.

Warnings

For external use only.

Do not use on damaged or broken skin.

When using this product keep out of eyes. Rinse with water to remove.

Stop use and ask a doctor if rash occurs.

Keep out of reach of children. If swallowed, get medical help or contact a Poison Control Center right away.

Directions

- Apply liberally 15 minutes before sun exposure
- reapply at least every 2 hours
- use a water-resistant sunscreen if swimming or sweating
- children under 6 months of age: ask a doctor
- Sun Protection Measures. Spending time in the sun increases your risk of skin cancer and early skin aging. To decrease this risk, regularly use a sunscreen with a broad spectrum SPF value of 15 or higher and other sun protection measures including:
- limit time in the sun, especially from 10 a..m. -2 p.m.
- wear long-sleeved shirts, pants, hats and sunglasses

Other information

Protect the product in this container from excessive heat and direct sun.

Inactive ingredients

Water, Isocetyl Stearate, Cetyl Dimethicone, Styrene/Acrylates Copolymer, Sorbitol, Ethyl Macadamiate, Cetearyl Alcohol, Dimethicone, Acrylates/Dimethicone Copolymer, Phenoxyethanol, Glyceryl Stearate, Glycerin, Hydroxyethyl Acrylate/Sodium Acryloyldimethyl Taurate Copolymer, PEG-100 Stearate, Ceteareth-10, Ethylhexyl Salicylate, VP/Eicosene Copolymer, Xanthan Gum, Polymethyl Methacrylate, Caprylyl Glycol, Cocos Nucifera (Coconut) Oil, Ethylhexylglycerin, Vaccinium Vitis-Idaea Fruit Extract, Quercus Suber Bark Extract, Triethoxycaprylylsilane, Camellia Sinensis Leaf Extract, Disodium EDTA, Tocopheryl Acetate, Oak Root Extract, Centella Asiatica Extract, Polygonum Aviculare Extract, Citric Acid, Gluconolactone, Isomalt, Calcium Gluconate, Lecithin, Vitis Vinifera (Grape) Fruit Cell Extract, Sodium Benzoate, Lepidium Sativum Sprout Extract.

Distributed by:

Roman Health Ventures, Inc.

900 Broadway, Suite 706A

New York, NY 10003

PACKAGE LABEL

roderm
Protecting SPF Lotion

Broad Spectrum SPF 28 Sunscreen

1.66 fl oz (50 mL)